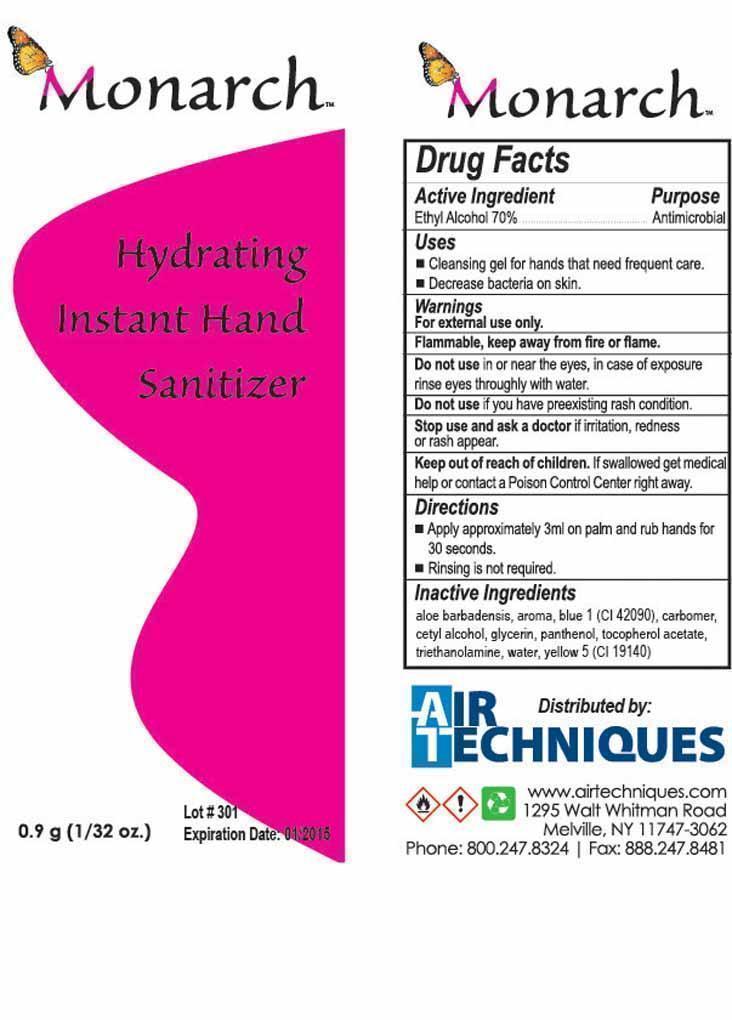 DRUG LABEL: Hydrating Instant Hand Sanitizer
NDC: 51811-659 | Form: GEL
Manufacturer: HANOVER PEN CORP dba HPC Global
Category: otc | Type: HUMAN OTC DRUG LABEL
Date: 20130201

ACTIVE INGREDIENTS: ALCOHOL .6329 mL/.9242 mL
INACTIVE INGREDIENTS: ALOE VERA FLOWER; FD&C BLUE NO. 1 ; CARBOMER INTERPOLYMER TYPE A (ALLYL SUCROSE CROSSLINKED) ; CETYL ALCOHOL; GLYCERIN; PANTHENOL; .ALPHA.-TOCOPHEROL ACETATE   ; TROLAMINE; WATER; FD&C YELLOW NO. 5

Drug Facts

Active Ingredient

Ethyl Alcohol 70 percent

Purpose

Antimicrobial

Uses

Cleansing gel for hands that need frequent care.

Decrease bacteria on skin.

Warnings

For external use only.

Flammable, keep away from fire or flame.

Do not use in or near the eyes, in case of exposure rinse eyes throughly with water.

Do not use if you have preexisting rash condition.

Stop use and ask a doctor if irritation, redness or rash appear.

Keep out of reach of children. If swallowed get medical help or contact Poison Control Center right away.

Directions

Apply approximately 3ml on palm and rub hands for 30 seconds.

Rinsing is not required.

Inactive Ingredients

aloe barbadensis, aroma, blue 1 (CI 42090), carbomer, cetyl alcohol, glycerin, panthenol, tocopherol acetate, triethanolamine, water, yellow 5 (CI 19140)

Drug Facts